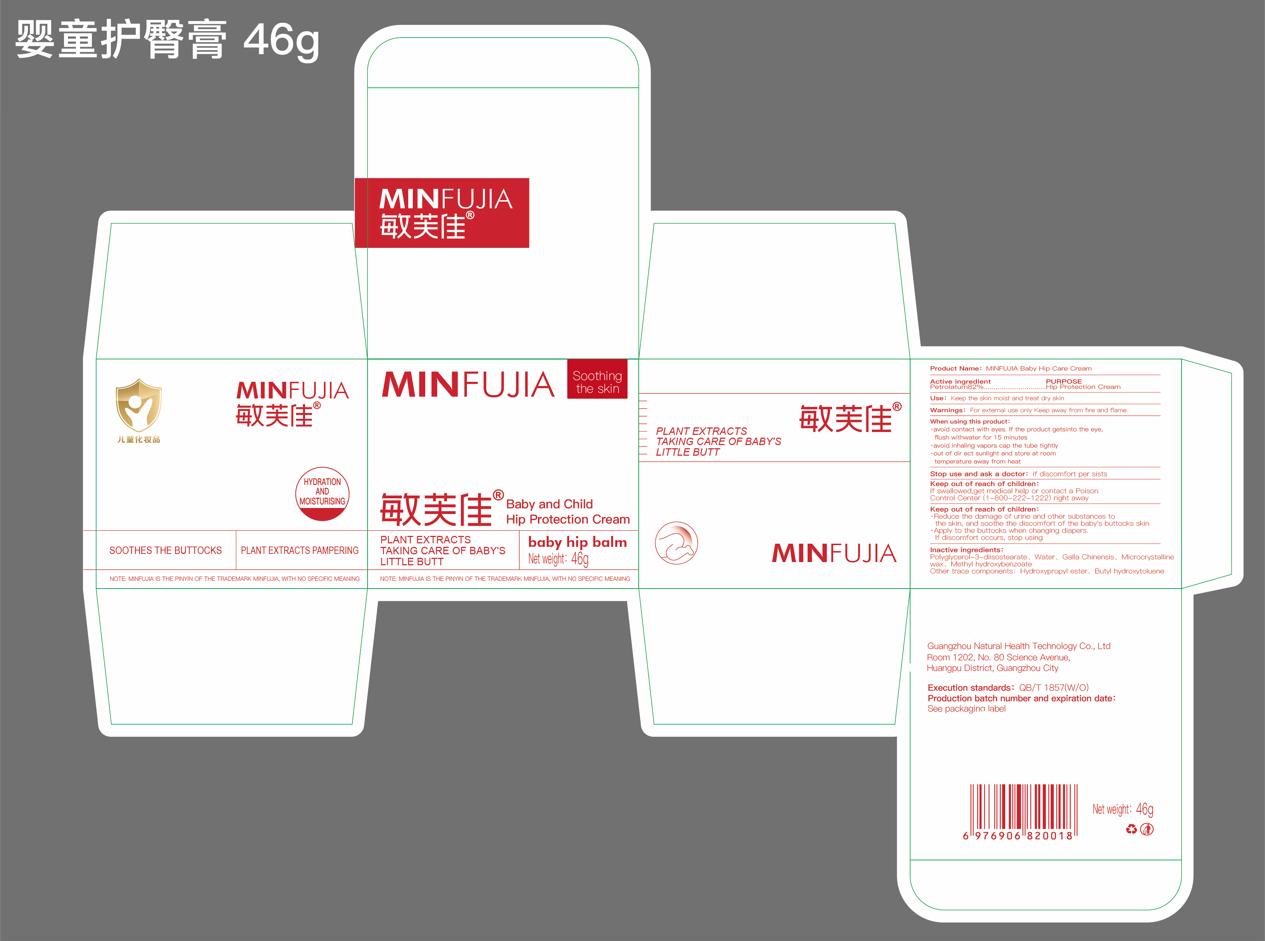 DRUG LABEL: MINFUJIA Baby and Child Hip Protection
NDC: 84634-003 | Form: CREAM
Manufacturer: Guangzhou Natural Health Technology Co., Ltd
Category: otc | Type: HUMAN OTC DRUG LABEL
Date: 20240815

ACTIVE INGREDIENTS: PETROLATUM 82 g/100 g
INACTIVE INGREDIENTS: MICROCRYSTALLINE WAX; POLYGLYCERYL-3 DIISOSTEARATE; WATER; (2-CHLOROPHENYL)METHYL 4-HYDROXYBENZOATE; BUTYLATED HYDROXYTOLUENE; 2-PROPENOIC ACID, 3-HYDROXYPROPYL ESTER; RHUS CHINENSIS WHOLE

ACTIVE INGREDIENT

Petrolatum 82%

PURPOSE

Hip Protection Cream

INDICATIONS AND USAGE

Keep the skin moist and treat dry skin

WARNINGS

For external use only Keep away from fire and flame.

When using this product:

·avoid contact with eyes. If the product getsinto the eye, flush withwater for 15 minutes

·avoid inhaling vapors cap the tube tightly

·out of dir ect sunlight and store at room temperature away from heat

Stop use and ask a doctor: if discomfort per sists

Keep out of reach of children: If swallowed,get medical help or contact a Poison Control Center (1–800–222–1222) right away

Keep out of reach of children:

·Reduce the damage of urine and other substances to the skin, and soothe the discomfort of the baby's buttocks skin

·Apply to the buttocks when changing diapers. If discomfort occurs, stop using

DOSAGE AND ADMINISTRATION

·Apply to the buttocks when changing diapers.If discomfort occurs, stop using

Inactive ingredients:

Polyglycerol-3-diisostearate, Water, Galla Chinensis, Microcrystalline wax, Methyl hydroxybenzoate

Other trace components: Hydroxypropyl ester、Butyl hydroxytoluene